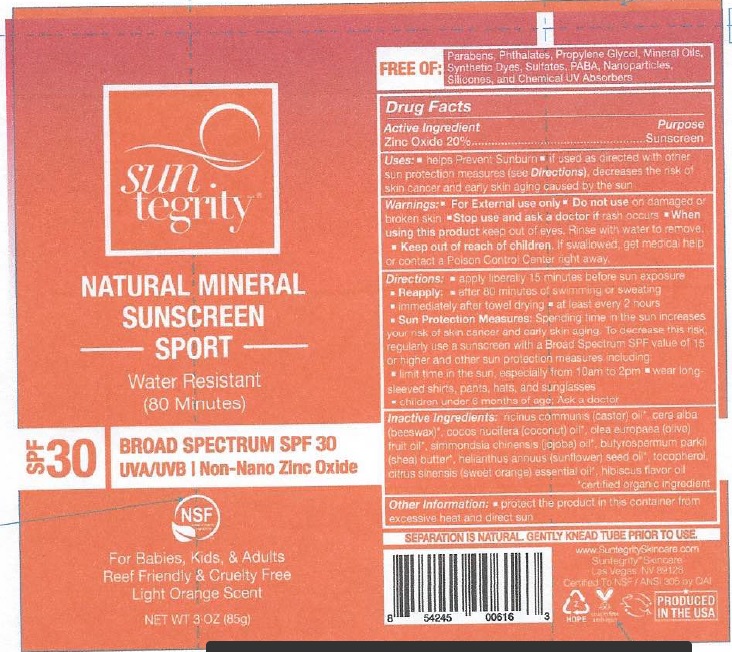 DRUG LABEL: SUNSCREEN
NDC: 62932-191 | Form: OIL
Manufacturer: Private Label Select Ltd CO
Category: otc | Type: HUMAN OTC DRUG LABEL
Date: 20200715

ACTIVE INGREDIENTS: ZINC OXIDE 20 g/100 g
INACTIVE INGREDIENTS: LINALOOL, (+/-)-; CASTOR OIL; OLIVE OIL; JOJOBA OIL; SUNFLOWER OIL; TOCOPHEROL; CITRUS SINENSIS FLOWER OIL; SHEA BUTTER; WHITE WAX; COCONUT OIL; .BETA.-CITRONELLOL, (+/-)-; GERANIOL

Suntegrity Natural Mineral Sunscreen SPF30